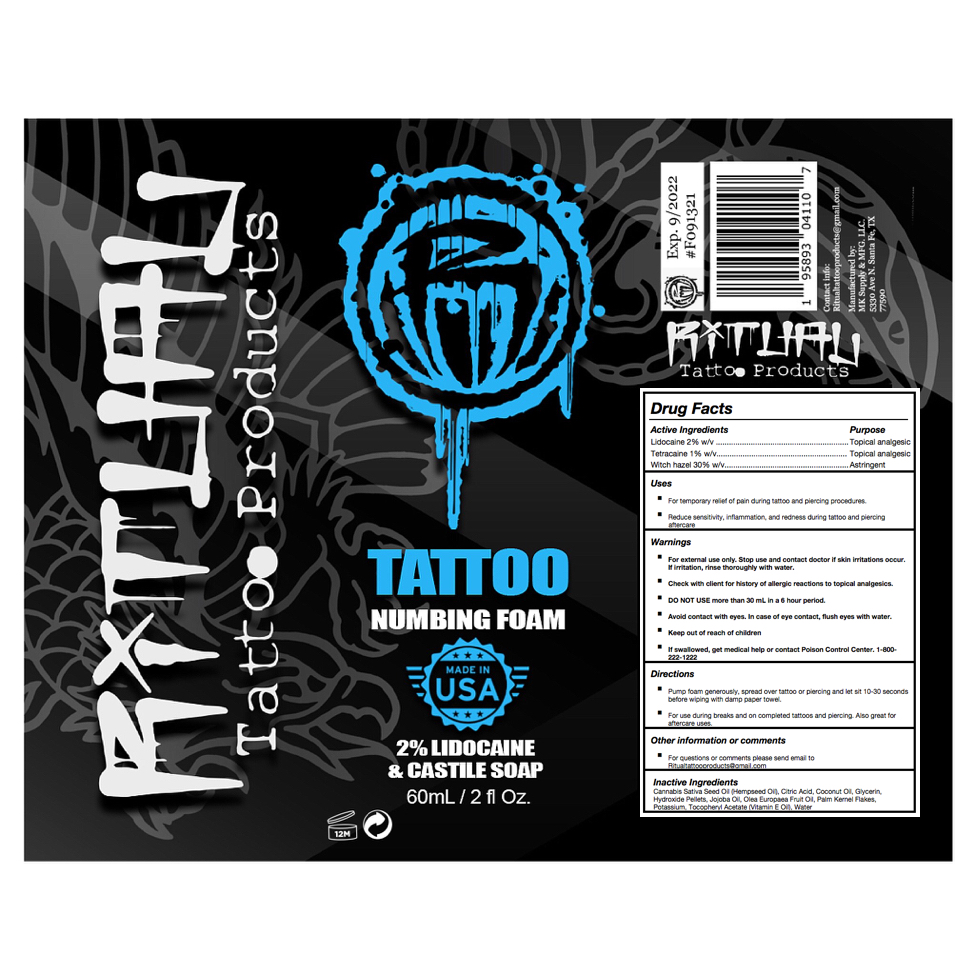 DRUG LABEL: Ritual Tattoo Reveal Foam
NDC: 82171-003 | Form: LIQUID
Manufacturer: MK Laboratory
Category: otc | Type: HUMAN OTC DRUG LABEL
Date: 20220201

ACTIVE INGREDIENTS: TETRACAINE 1 g/100 mL; WITCH HAZEL 30 g/100 mL; LIDOCAINE 2 g/100 mL
INACTIVE INGREDIENTS: GLYCERIN; PALM KERNEL OIL; POTASSIUM HYDROXIDE; OLEA EUROPAEA (OLIVE) OIL UNSAPONIFIABLES; .ALPHA.-TOCOPHEROL ACETATE; CITRIC ACID MONOHYDRATE; CANNABIS SATIVA SEED OIL; JOJOBA OIL; WATER; COCONUT OIL

Ritual Tattoo Reveal Foam

Active Ingredients

Lidocaine 2% w/v. Purpose: Topical analgesic

Tetracaine 1% w/v. Purpose: Topical analgesic

Witch Hazel 30% w/v. Purpose: Astringent

Purpose

Lidocaine 2% w/v. Purpose: Topical analgesic

Tetracaine 1% w/v. Purpose: Topical analgesic

Witch Hazel 30% w/v. Purpose: Astringent

Uses

- For temporary relief of pain during tattoo and piercing procedures.
- Reduce sensitivity, inflammation, and redness during tattoo and piercing aftercare

Warnings

- For external use only.
- Check with client for history of allergic reactions to topical analgesics.

DO NOT USE more than 30 mL in a 6 hour period.

WHEN USING

- Avoid contact with eyes. In case of eye contact, flush eyes with water.

- Stop use and contact doctor if skin irritations occur. If irritation, rinse thoroughly with water.
- If swallowed, get medical help or contact Poison Control Center. 1-800-222-1222

Keep out of reach of children

Directions

- Pump foam generously, spread over tattoo or piercing and let sit 10-30 seconds before wiping with damp paper towel.
- For use during breaks and on completed tattoos and piercing. Also great for aftercare uses.

Other Information or Comments

For questions or comments please send email to Ritualtattooproducts@gmail.com

Inactive Ingredients

Cannabis Sativa Seed Oil (Hempseed Oil), Citric Acid, Coconut Oil, Glycerin, Hydroxide Pellets, Jojoba Oil, Olea Europaea Fruit Oil, Palm Kernel Flakes, Potassium, Tocopheryl Acetate (Vitamin E Oil), Water

Principal Display Panel

250 mL NDC: 82171-003-60